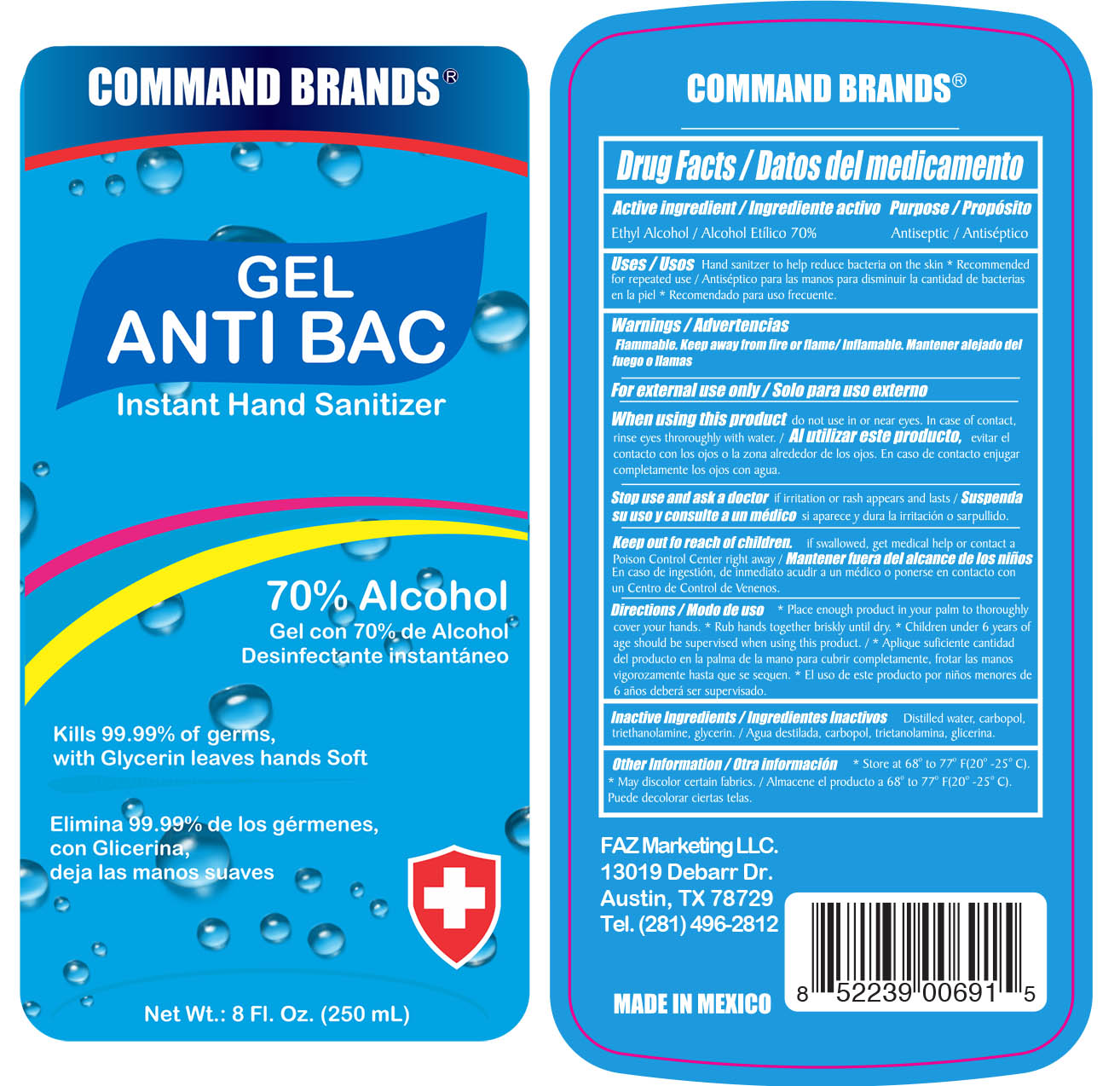 DRUG LABEL: Hand Sanitizer
NDC: 50061-002 | Form: GEL
Manufacturer: FAZ Marketing
Category: otc | Type: HUMAN OTC DRUG LABEL
Date: 20200629

ACTIVE INGREDIENTS: ALCOHOL 70 mL/100 mL
INACTIVE INGREDIENTS: GLYCERIN; TROLAMINE; WATER; CARBOMER HOMOPOLYMER, UNSPECIFIED TYPE

Command Brands FAZCquib Hand Sanitizer

Active Ingredient/Ingrediente Activo

Ethyl Alcohol/Aclohol Etílico 70%

Purpose/Propósito

Antimicrobial/Amtimicrobiano

Uses/Usos

■ Hand sanitizer to help reduce bacteria on the skin * Recommended for repeated use/Antiséptico para las manos para disminuir la cantidad de bacteria en la piel * Recomendado para uso frecuente.

Warnings/Advertencias

Flammable. Keep away from fire or flame / Inflamable. Manterner alejado del fuego o llamas.

For external use only / Solo para uso externo

When using this product/Al utilizar este producto

■do not use in or near eyes. In case of contact, rinse eyes thoroughly with water./evitar el contacto con los ojos o la zona alrededor de los ojos. En caso de contacto enjuagar completamente los ojos con agua.

Stop use and ask a doctor if/Suspenda su uso y consulte a un médico

■ if irritation or rash appears and lasts/si aparece y dura irritación o sarpullido.

Keep out of reach of children/Mantener fuera del alcance de los niños.

If swallowed, get medical help or Poison Control Center right away./En caso de ingestión, de inmediato acudir a un médico o ponerse en contacto con un Centro de Control de Venenos.

Directions/Modo de uso

■Place enough product in your palm to thoroughly cover your hands. * Rub hands together briskly until dry. * Children under 6 years of age should be supervised when using this product/* Aplique suficiente cantidad del producto en la palma de la mano para cubrir completamente. * Frotar las manos vigorosamente hasta que se sequen. * El uso de este producto por niños menores de 6 años deberá ser supervisado.

Inactive Ingredients/Ingredientes inactivos

Distilled water, carbopol, triethanolamine, glycerin/Agua destilada, carbopol, trietanolamina, glicerina.

Other information/Otra Información

■ Store at 68° to 77° F (20° - 25° C). * May discolor certain fabrics. / Almacene el producto a 68° to 77° F (20° - 25° C). * Puede decolorar ciertas telas.